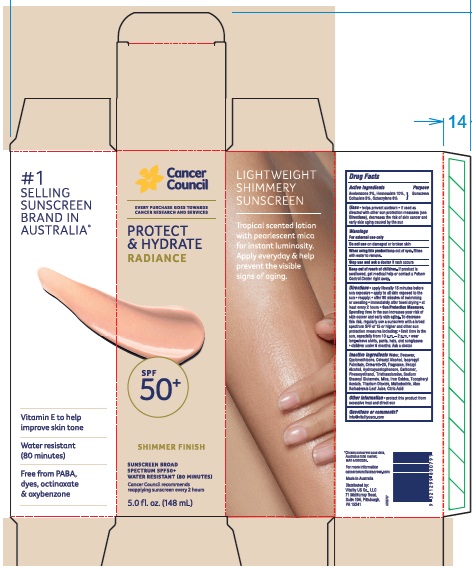 DRUG LABEL: Cancer Council Protect and Hydrate Radiance SPF50 Plus
NDC: 84258-002 | Form: LOTION
Manufacturer: Vitality US Co.
Category: otc | Type: HUMAN OTC DRUG LABEL
Date: 20240415

ACTIVE INGREDIENTS: HOMOSALATE 100 mg/1 mL; OCTOCRYLENE 80 mg/1 mL; OCTISALATE 50 mg/1 mL; AVOBENZONE 30 mg/1 mL
INACTIVE INGREDIENTS: .ALPHA.-TOCOPHEROL ACETATE; YELLOW WAX; CETOSTEARYL ALCOHOL; TROLAMINE; WATER; CYCLOMETHICONE; ALOE VERA LEAF; FERROSOFERRIC OXIDE; POLYOXYL 20 CETOSTEARYL ETHER; MICA; TITANIUM DIOXIDE; CITRIC ACID MONOHYDRATE; PHENOXYETHANOL; HYDROXYACETOPHENONE; CARBOMER HOMOPOLYMER, UNSPECIFIED TYPE; SODIUM STEAROYL GLUTAMATE; FERRIC OXIDE RED; BENZYL ALCOHOL; MALTODEXTRIN; FERRIC OXIDE YELLOW; ISOPROPYL PALMITATE

Cancer Council Protect and Hydrate Radiance SPF50 Plus

Active Ingredients

Avobenzone 3%

Homosalate 10%

Octisalate 5%

Octocrylene 8%

Purpose

Sunscreen

Uses

- helps prevent sunburn
- if used as directed with other sun protection measures (see Directions), decreases the risk of skin cancer and early skin aging caused by the sun

Warnings

For external use only

Do not use

on damaged or broken skin

When using this product

keep out of eyes. Rinse with water to remove.

Stop use and ask a doctor

if rash occurs

Keep out of reach of children.

If product is swallowed, get medical help or contact a Poison Control Center right away.

Directions

- apply liberally 15 minutes before sun exposure
- apply to all skin exposed to the sun
- reapply:
- after 80 minutes of swimming or sweating
- immediately after towel drying
- at least every 2 hours
- Sun Protection Measures. Spending time in the sun increases your risk of skin cancer and early skin aging. To decrease this risk, regularly use a sunscreen with a broad spectrum SPF of 15 or higher and other sun protection measures including:
- limit time in the sun, especially from 10 a.m. - 2 p.m.
- wear long-sleeve shirts, pants, hats, and sunglasses
- children under 6 months: Ask a doctor

Inactive ingredients

Water, Beeswax, Cyclomethicone, Cetearyl Alcohol, Isopropyl Palmitate, Ceteareth-20, Fragrance, Benzyl Alcohol, Hydroxyacetophenone, Carbomer, Phenoxyethanol, Triethanolamine, Sodium Stearoyl Glutamate, Mica, Iron Oxides, Tocopheryl Acetate, Titanium Dioxide, Maltodextrin, Aloe Barbadensis Leaf Juice, Citric Acid

Other information

- protect this product from excessive heat and direct sun

Questions or comments?

info@vitalityusco.com